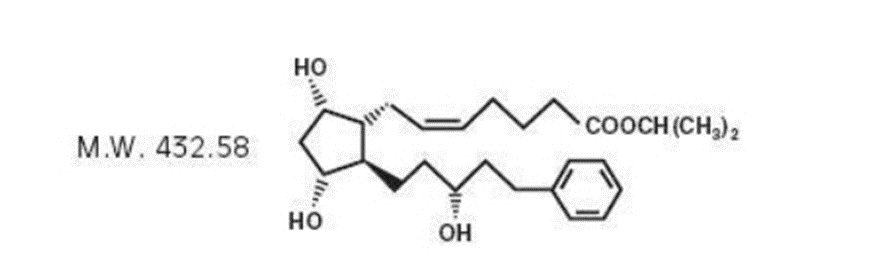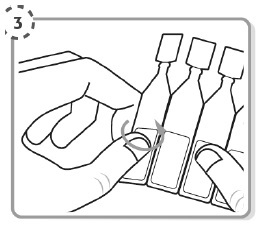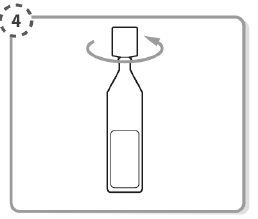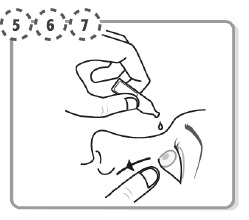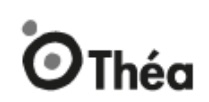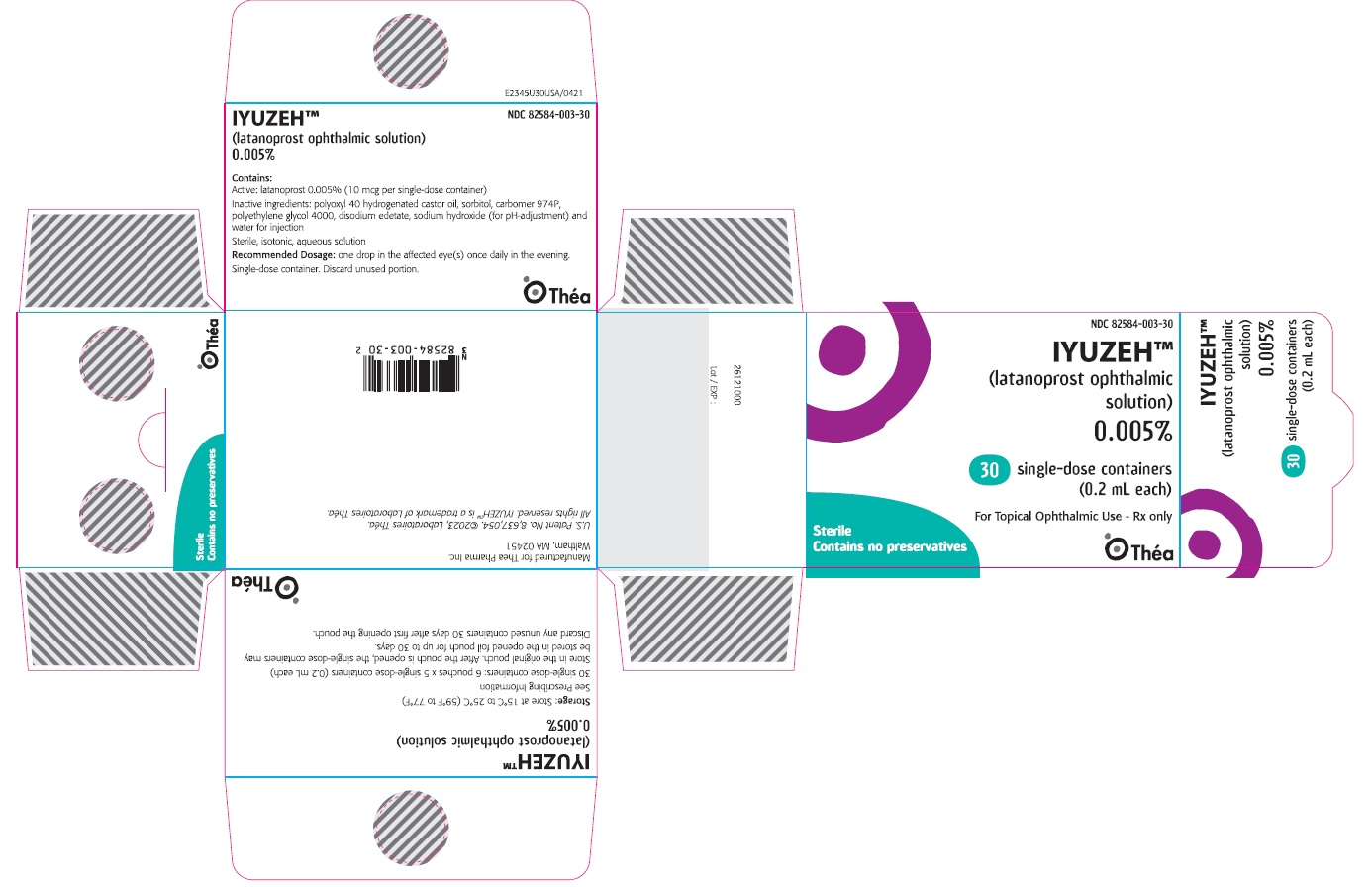 DRUG LABEL: IYUZEH
NDC: 82584-003 | Form: SOLUTION/ DROPS
Manufacturer: Thea Pharma Inc.
Category: prescription | Type: HUMAN PRESCRIPTION DRUG LABEL
Date: 20240730

ACTIVE INGREDIENTS: LATANOPROST 50 ug/1 mL
INACTIVE INGREDIENTS: SORBITOL; CARBOMER HOMOPOLYMER TYPE B (ALLYL PENTAERYTHRITOL CROSSLINKED); POLYOXYL 40 HYDROGENATED CASTOR OIL; POLYETHYLENE GLYCOL 4000; EDETATE DISODIUM; SODIUM HYDROXIDE; WATER

HIGHLIGHTS OF PRESCRIBING INFORMATION

These highlights do not include all the information needed to use IYUZEH safely and effectively. See full prescribing information for IYUZEH.
IYUZEH (latanoprost ophthalmic solution) 0.005%, for topical ophthalmic use
Initial U.S. Approval: 1996

1 INDICATIONS AND USAGE

IYUZEH is a prostaglandin F2α analogue indicated for the reduction of elevated intraocular pressure in patients with open-angle glaucoma or ocular hypertension. (1)

2 DOSAGE AND ADMINISTRATION

One drop in the affected eye(s) once daily in the evening. (2)

3 DOSAGE FORMS AND STRENGTHS

Ophthalmic solution containing latanoprost 0.005% (50 mcg/mL). (3)

4 CONTRAINDICATIONS

Known hypersensitivity to latanoprost or any other ingredients in this product. (4)

5 WARNINGS AND PRECAUTIONS

- Pigmentation: Pigmentation of the iris, periorbital tissue (eyelid) and eyelashes can occur. Iris pigmentation likely to be permanent. (5.1)
- Eyelash Changes: Gradual change to eyelashes including increased length, thickness and number of lashes. Usually, reversible. (5.2)

6 ADVERSE REACTIONS

Most common adverse reactions (5% to 35%) for IYUZEH are: conjunctival hyperemia, eye irritation, eye pruritus, abnormal sensation in eye, foreign body sensation in eyes, vision blurred and lacrimation increased. (6.1)

To report SUSPECTED ADVERSE REACTIONS, contact Thea Pharma Inc. at 1-833-838-4028 or FDA at 1-800-FDA-1088 or www.fda.gov/medwatch.

See 17 for PATIENT COUNSELING INFORMATION.

Revised: 03/2024

FULL PRESCRIBING INFORMATION

1 INDICATIONS AND USAGE

IYUZEH™ (latanoprost ophthalmic solution) 0.005% is indicated for the reduction of elevated intraocular pressure (IOP) in patients with open-angle glaucoma or ocular hypertension.

2 DOSAGE AND ADMINISTRATION

The recommended dosage is one drop in the affected eye(s) once daily in the evening. If one dose is missed, treatment should continue with the next dose as normal.

The dosage of IYUZEH should not exceed once daily; the combined use of two or more prostaglandins, or prostaglandin analogs including IYUZEH is not recommended. It has been shown that administration of these prostaglandin drug products more than once daily may decrease the IOP lowering effect or cause paradoxical elevations in IOP.

Reduction of the IOP starts approximately 3 to 4 hours after administration and the maximum effect is reached after 8 to 12 hours.

IYUZEH may be used concomitantly with other topical ophthalmic drug products to lower IOP. In vitro studies have shown that precipitation occurs when eye drops containing thimerosal are mixed with the preserved 0.005% latanoprost reference product. If more than one topical ophthalmic drug is being used, the drugs should be administered at least five (5) minutes apart. Contact lenses should be removed prior to the administration of IYUZEH and may be reinserted 15 minutes after administration.

The solution from one individual unit is to be used immediately after opening for administration to one or both eyes. Since sterility cannot be maintained after the individual unit is opened, the remaining contents should be discarded immediately after administration.

3 DOSAGE FORMS AND STRENGTHS

Ophthalmic solution: opalescent, white to slightly yellow solution containing latanoprost 0.005% (50 mcg/mL).

4 CONTRAINDICATIONS

Known hypersensitivity to latanoprost or any other ingredients in this product.

5 WARNINGS AND PRECAUTIONS

5.1 Pigmentation

Topical latanoprost ophthalmic products, including IYUZEH have been reported to cause changes to pigmented tissues. The most frequently reported changes have been increased pigmentation of the iris, periorbital tissue (eyelid), and eyelashes. Pigmentation is expected to increase as long as latanoprost is administered.

The pigmentation change is due to increased melanin content in the melanocytes rather than to an increase in the number of melanocytes. After discontinuation of latanoprost, pigmentation of the iris is likely to be permanent, while pigmentation of the periorbital tissue and eyelash changes have been reported to be reversible in some patients. Patients who receive treatment should be informed of the possibility of increased pigmentation. The long-term effects of increased pigmentation are not known.

Iris color change may not be noticeable for several months to years. Typically, the brown pigmentation around the pupil spreads concentrically towards the periphery of the iris and the entire iris or parts of the iris become more brownish. Neither nevi nor freckles of the iris appear to be affected by treatment. While treatment with IYUZEH can be continued in patients who develop noticeably increased iris pigmentation, these patients should be examined regularly.

5.2 Eyelash Changes

Latanoprost ophthalmic products, including IYUZEH may gradually change eyelashes and vellus hair in the treated eye; these changes include increased length, thickness, pigmentation, the number of lashes or hairs, and misdirected growth of eyelashes. Eyelash changes are usually reversible upon discontinuation of treatment.

5.3 Intraocular Inflammation

IYUZEH should be used with caution in patients with a history of intraocular inflammation (iritis/uveitis) and should generally not be used in patients with active intraocular inflammation because inflammation may be exacerbated.

5.4 Macular Edema

Macular edema, including cystoid macular edema, has been reported during treatment with latanoprost ophthalmic products, including IYUZEH. IYUZEH should be used with caution in aphakic patients, in pseudophakic patients with a torn posterior lens capsule, or in patients with known risk factors for macular edema.

5.5 Herpetic Keratitis

Reactivation of herpes simplex keratitis has been reported during treatment with latanoprost. IYUZEH should be used with caution in patients with a history of herpetic keratitis. IYUZEH should be avoided in cases of active herpes simplex keratitis because inflammation may be exacerbated.

5.6 Contact Lens Use

Contact lenses should be removed prior to the administration of IYUZEH and may be reinserted 15 minutes after administration.

6 ADVERSE REACTIONS

The following adverse reactions have been reported with the use of topical latanoprost products and are discussed in greater detail in other sections of the label:

- Iris pigmentation changes [see Warnings and Precautions (5.1)]
- Eyelid skin darkening [see Warnings and Precautions (5.1)]
- Eyelash changes (increased length, thickness, pigmentation, and number of lashes) [see Warnings and Precautions (5.2)]
- Intraocular inflammation (iritis/uveitis) [see Warnings and Precautions (5.3)]
- Macular edema, including cystoid macular edema [see Warnings and Precautions (5.4)]

6.1 Clinical Trials Experience

Because clinical trials are conducted under widely varying conditions, adverse reaction rates observed in the clinical trials of a drug cannot be directly compared to rates in the clinical trials of another drug and may not reflect the rates observed in practice.

In the two clinical trials conducted with IYUZEH (latanoprost ophthalmic solution) 0.005% comparing it to XALATAN the preserved 0.005% latanoprost reference product, the most frequently reported ocular adverse reactions were conjunctival hyperemia and eye irritation (Table 1).

Table 1. Ocular Adverse Reactions Reported by ≥ 1% of Subjects Receiving IYUZEH
Symptom/Finding | Adverse Reactions (incidence (%))
Symptom/Finding | IYUZEH (n=378) | XALATAN (n=358)
Conjunctival hyperemia | 129 (34) | 133 (37)
Eye irritation | 72 (19) | 112 (31)
Eye pruritus | 57 (15) | 58 (16)
Abnormal sensation in eye | 51 (14) | 52 (15)
Foreign body sensation in eyes | 44 (12) | 36 (10)
Vision blurred | 28 (7) | 30 (8)
Lacrimation increased | 19 (5) | 14 (4)
Photophobia | 13 (3) | 17 (5)

6.2 Postmarketing Experience

The following adverse reactions have been identified during post-approval use of topical latanoprost products. Because these reactions are reported voluntarily from a population of uncertain size, it is not always possible to reliably estimate their frequency or establish a causal relationship to drug exposure. The reactions, which have been chosen for inclusion due to either their seriousness, frequency of reporting, possible causal connection to ophthalmic latanoprost products, or a combination of these factors, include:

- Nervous System Disorders: Dizziness; headache; toxic epidermal necrolysis
- Eye Disorders: Eyelash and vellus hair changes of the eyelid (increased length, thickness, pigmentation, and number of eyelashes); keratitis; corneal edema and erosions; intraocular inflammation (iritis/uveitis); macular edema, including cystoid macular edema; trichiasis; periorbital and lid changes resulting in deepening of the eyelid sulcus; iris cyst; eyelid skin darkening; localized skin reaction on the eyelids; conjunctivitis; pseudopemphigoid of the ocular conjunctiva.
- Respiratory, Thoracic and Mediastinal Disorders: Asthma and exacerbation of asthma; dyspnea
- Gastrointesting Disorders: Nausea; vomiting
- Skin and Subcutaneous Tissue Disorders: Pruritis
- Infections and Infestations: Herpes keratitis
- Cardiac Disorders: Angina; palpitations; angina unstable
- General Disorders and Administration Site Conditions: Chest pain

7 DRUG INTERACTIONS

The combined use of two or more prostaglandins, or prostaglandin analogs including IYUZEH is not recommended. It has been shown that administration of these prostaglandin drug products more than once daily may decrease the IOP lowering effect or cause paradoxical elevations in IOP.

8 USE IN SPECIFIC POPULATIONS

8.1 Pregnancy

Risk Summary

There are no adequate and well-controlled studies of IYUZEH administration in pregnant women to inform drug-associated risks.

In animal reproduction studies, intravenous (IV) administration of latanoprost to pregnant rabbits and rats throughout the period of organogenesis produced malformations, embryofetal lethality and spontaneous abortion at clinically relevant doses (equivalent to 1.3 – 324 times the maximum recommended human ophthalmic dose, on a mg/m^2 basis, assuming 100% absorption) (see Data) .

The background risk of major birth defects and miscarriage for the indicated population is unknown. However, the background risk in the U.S. general population of major birth defects is 2 to 4%, and of miscarriage is 15 to 20% of clinically recognized pregnancies.

Data
Animal Data
Embryofetal studies were conducted in pregnant rabbits administered latanoprost daily by IV injection on gestation days 6 through 18, to target the period of organogenesis. A no observed adverse effect level (NOAEL) was not established for rabbit developmental toxicity. Post-implantation loss due to late resorption was shown as doses ≥0.2 mcg/kg/day (equivalent to 1.3 times the maximum recommended human ophthalmic dose [RHOD], on a mg/m^2 basis, assuming 100% absorption). Spina bifida and abortion occurred at 5 mcg/kg/day (equivalent to 32 times the maximum RHOD). Total litter loss due to early resorption was observed at doses ≥50 mcg/kg/day (324 times the maximum RHOD). Transient signs of maternal toxicity were observed after IV dosing (increased breathing, muscle tremors, slight motor incoordination) at 300 mcg/kg/day (1946 times the maximum RHOD). No maternal toxicity was observed at doses up to 50 mcg/kg/day.

Embryofetal studies were conducted in pregnant rats administered latanoprost daily by IV injection on gestation days 6 through 15, to target the period of organogenesis. A NOAEL for rat developmental toxicity was not established. Cleft palate was observed at 1 mcg/kg (equivalent to 3.2 times the maximum RHOD, on a mg/m^2 basis, assuming 100% absorption). Brain porencephalic cyst(s) were observed ≥50 mcg/kg (162 times the maximum RHOD). Skeletal anomalies were observed at 250 mcg/kg (811 times the maximum RHOD). No maternal toxicity was detectable at 250 mcg/kg/day.

Prenatal and postnatal development was assessed in rats. Pregnant rats were administered latanoprost daily by IV injection from gestation day 15, through delivery, until weaning (lactation Day 21). No adverse effects on rat offspring were observed at doses up to 10 mcg/kg/day (32 times the maximum RHOD, on a mg/m2 basis, assuming 100% absorption). At 100 mcg/kg/day (324 times the maximum RHOD), maternal deaths and pup mortality occurred.

8.2 Lactation

Risk Summary

It is not known whether this drug or its metabolites are excreted in human milk. Because many drugs are excreted in human milk, caution should be exercised when IYUZEH is administered to a nursing woman.

The developmental and health benefits of breastfeeding should be considered along with the mother’s clinical need for IYUZEH and any potential adverse effects on the breastfed child from IYUZEH.

8.4 Pediatric Use

The safety and effectiveness of IYUZEH have not been established in pediatric patients.

8.5 Geriatric Use

No overall differences in safety or effectiveness have been observed between elderly and younger adult patients.

10 OVERDOSAGE

Intravenous infusion of up to 3 mcg/kg of latanoprost in healthy volunteers produced mean plasma concentrations 200 times higher than during clinical treatment with latanoprost ophthalmic solution and no adverse reactions were observed. IV dosages of 5.5 to 10 mcg/kg caused abdominal pain, dizziness, fatigue, hot flushes, nausea, and sweating.

11 DESCRIPTION

Latanoprost is a prostaglandin F2α analogue. Its chemical name is isopropyl-(Z)-7[(1R,2R,3R,5S)3,5dihydroxy-2-[(3R)-3-hydroxy-5-phenylpentyl]cyclopentyl]-5-heptenoate. Its molecular formula is C26H40O5 and its chemical structure is:

Latanoprost is a colorless to yellow oil that is very soluble in acetonitrile and freely soluble in ethanol, ethyl acetate, and methanol. It is practically insoluble in water and hexanes.

IYUZEH (latanoprost ophthalmic solution) 0.005% is supplied as a sterile, isotonic, aqueous solution of latanoprost with a pH of approximately 7 and an osmolality of approximately 280 mOsmol/kg. Each mL of IYUZEH contains 50 mcg of latanoprost. The inactive ingredients are: polyoxyl 40 hydrogenated castor oil, sorbitol, carbomer 974P, polyethylene glycol 4000, disodium edetate, sodium hydroxide (for pH-adjustment) and water for injections. One drop contains approximately 1.5 mcg of latanoprost.

IYUZEH does not contain a preservative.

12 CLINICAL PHARMACOLOGY

12.1 Mechanism of Action

Latanoprost is a prostaglandin F2α analogue that is believed to reduce the IOP by increasing the outflow of aqueous humor. Studies in animals and man suggest that the main mechanism of action is increased uveoscleral outflow. Elevated IOP represents a major risk factor for glaucomatous field loss. The higher the level of IOP, the greater the likelihood of optic nerve damage and visual field loss.

12.2 Pharmacodynamics

Reduction of the IOP in man starts about 3-4 hours after administration and maximum effect is reached after 8-12 hours. IOP reduction is present for at least 24 hours.

12.3 Pharmacokinetics

Absorption

Latanoprost is absorbed through the cornea where the isopropyl ester prodrug is hydrolyzed to the acid form to become biologically active.

Distribution

The distribution volume in humans is 0.16 ± 0.02 L/kg. The acid of latanoprost can be measured in aqueous humor during the first 4 hours, and in plasma only during the first hour after local administration. Studies in man indicate that the peak concentration in the aqueous humor is reached about two hours after topical administration.

Elimination

Metabolism
Latanoprost, an isopropyl ester prodrug, is hydrolyzed by esterases in the cornea to the biologically active acid. The active acid of latanoprost reaching the systemic circulation is primarily metabolized by the liver to the 1,2-dinor and 1,2,3,4-tetranor metabolites via fatty acid β-oxidation.

Excretion
The elimination of the acid of latanoprost from human plasma is rapid (t1/2 = 17 min) after both IV and topical administration. Systemic clearance is approximately 7 mL/min/kg. Following hepatic β-oxidation, the metabolites are mainly eliminated via the kidneys. Approximately 88% and 98% of the administered dose are recovered in the urine after topical and IV dosing, respectively.

13 NONCLINICAL TOXICOLOGY

13.1 Carcinogenesis, Mutagenesis, Impairment of Fertility

Carcinogenesis

Latanoprost was not carcinogenic in either mice or rats when administered by oral gavage at doses of up to 170 mcg/kg/day (approximately 2800 times the recommended maximum human dose) for up to 20 and 24 months, respectively.

Mutagenesis

Latanoprost was not mutagenic in bacteria, in mouse lymphoma, or in mouse micronucleus tests. Chromosome aberrations were observed in vitro with human lymphocytes. Additional in vitro and in vivo studies on unscheduled DNA synthesis in rats were negative.

Impairment of Fertility

Latanoprost has not been found to have any effect on male or female fertility in rat studies at IV doses up to 250 mcg/kg/day (811 times the maximum RHOD, on a mg/m^2 basis, assuming 100% absorption).

14 CLINICAL STUDIES

14.1 Elevated Baseline IOP

In randomized, controlled clinical trials of patients with open angle glaucoma or ocular hypertension with mean baseline IOP of 19 - 24 mmHg, IYUZEH lowered IOP by 3 – 8 mmHg versus 4 – 8 mmHg by latanoprost ophthalmic solution preserved with benzalkonium chloride. Latanoprost ophthalmic solution preserved with benzalkonium chloride was approximately 1 mmHg more effective than IYUZEH.

16 HOW SUPPLIED/STORAGE AND HANDLING

IYUZEH (latanoprost ophthalmic solution) is an opalescent, isotonic, white to slightly yellow solution of latanoprost 50 mcg/mL (0.005%) practically free from foreign particles.

It is supplied as a sterile solution in translucent low-density polyethylene single-dose container packaged in foil pouches (5 single-dose containers per pouch).

NDC 82584-003-30; Unit-of-Use Carton of 30

Storage:

Store at 15°C to 25°C (59°F to 77°F).

Store in the original pouch. After the pouch is opened, the single-dose containers may be stored in the opened foil pouch for up to 30 days at room temperature 15°C to 25°C (59°F to 77°F).

Patient should be advised to write down the date the foil pouch is opened in the space provided on the pouch.

Discard any unused containers 30 days after first opening the pouch.

17 PATIENT COUNSELING INFORMATION

Potential for Pigmentation

Advise patients about the potential for increased brown pigmentation of the iris, which may be permanent. Inform patients about the possibility of eyelid skin darkening, which may be reversible after discontinuation of IYUZEH.

Potential for Eyelash Changes

Inform patients of the possibility of eyelash and vellus hair changes in the treated eye during treatment with latanoprost ophthalmic solution. These changes may result in a disparity between eyes in length, thickness, pigmentation, number of eyelashes or vellus hairs, and/or direction of eyelash growth. Eyelash changes are usually reversible upon discontinuation of treatment.

Handling the Container

Advise patients that IYUZEH is a sterile solution that does not contain a preservative. The drops are supplied in single-dose container. The solution from one individual container is to be used immediately after opening for administration to one or both eyes. Since sterility cannot be maintained after the individual container is opened, the remaining contents should be discarded immediately after administration. Open a new single-dose container every time you use IYUZEH.

When to Seek Physician Advice

Advise patients that if they develop an intercurrent ocular condition (e.g., trauma or infection) or have ocular surgery, or develop any ocular reactions, particularly conjunctivitis and eyelid reactions, they should immediately seek their physician’s advice concerning the continued use of IYUZEH.

Contact Lens Use

Advise patients that contact lenses should be removed prior to administration of the solution. Lenses may be reinserted 15 minutes following administration of IYUZEH.

Use with Other Ophthalmic Drugs

Advise patients that if more than one topical ophthalmic drug is being used, the drugs should be administered at least five (5) minutes apart.

If a Dose is Missed

Advise patients that if one dose is missed, treatment should continue with the next dose as normal.

Manufactured for: Thea Pharma Inc. Waltham, MA 02451.

All rights reserved.

U.S. Patent N°. 8,637,054. ©2021, Laboratoires Théa. All rights reserved. IYUZEH™ is a trademark of Laboratoires Théa.

PATIENT INFORMATION
IYUZEH™ (eye yoo’ zeh)
(latanoprost ophthalmic solution) 0.005%
For topical ophthalmic use

What is IYUZEH?

IYUZEH is a prescription sterile eye drop solution which does not contain a preservative. IYUZEH is used to lower the pressure in the eye (intraocular pressure) in people with open-angle glaucoma or ocular hypertension when their eye pressure is too high. IYUZEH belongs to a group of medicines called prostaglandin analogs.
It is not known if IYUZEH is safe and effective in children.

Do not use IYUZEH if you are allergic to latanoprost or any of the ingredients in IYUZEH. See the end of this Patient Information leaflet for a complete list of ingredients in IYUZEH.

Before you use IYUZEH, tell your doctor if you:

- have or have had eye problems including any surgery on your eye or eyes
- are using any other eye medicines
- have any other medical problems
- are pregnant or plan to become pregnant. It is not known if IYUZEH will harm your unborn baby. If you become pregnant while using IYUZEH talk to your doctor right away.
- are breastfeeding or plan to breastfeed. It is not known if IYUZEH passes into your breast milk. Talk to your doctor about the best way to feed your baby if you use IYUZEH.

Tell your doctor about all the medicines you take, including prescription and over-the-counter medicines, vitamins, and herbal supplements.

Know the medicines you take. Keep a list of them to show your doctor and pharmacist when you get a new medicine.

How should I take IYUZEH?

Read the Instructions for Use at the end of this Patient Information leaflet for additional instructions about the right way to use IYUZEH.

- Use 1 drop of IYUZEH in your eye (or eyes) each evening. Talk to your doctor or pharmacist if you are not sure how to use IYUZEH.
- Your IYUZEH may not work as well if you use it more than 1 time each evening.
- If you miss a dose of IYUZEH, skip the missed dose and take the next dose at your regular time.
- If you use other medicines in your eye, wait at least 5 minutes between using IYUZEH and your other eye medicines.
- Contact lenses should be taken out before using IYUZEH and you should wait at least 15 minutes after giving the dose of IYUZEH before putting the contact lenses back into your eyes.
- Use your IYUZEH right away after opening. Each IYUZEH single-dose container is sterile and is to be used 1 time then thrown away. Do not save any IYUZEH that may be left over after you use your medicine. Using IYUZEH that is not sterile may cause other eye problems.

What are the possible side effects of IYUZEH?

IYUZEH may cause serious side effects including:

- changes in the color of your eye (iris). Your iris may become more brown in color while using IYUZEH. This color change may not go away when you stop using IYUZEH. If IYUZEH is used in 1 eye only, the color of that eye may always be a different color from the color of your other eye.
- darkening of the color of the skin around your eye (eyelid). These skin changes usually go away when you stop using IYUZEH.
- increasing the length, thickness, color, or number of your eyelashes. These eyelash changes usually go away when you stop using IYUZEH.
- hair growth on your eyelids. This hair growth usually goes away when you stop using IYUZEH.

The most common side effects of IYUZEH include:

- redness of and around the eye (conjunctival hyperemia)
- eye irritation
- eye itching

- abnormal sensation in the eye
- foreign body sensation in the eye
- blurry vision
- increase of tears in the eye (increased lacrimation)

Tell your doctor right away if you have any new eye problems while using IYUZEH, including:

- an eye injury
- an eye infection
- a sudden loss of vision
- eye surgery
- swelling and redness of and around your eye (conjunctivitis)
- problems with your eyelids

Additionally, the following side effects have been reported in other latanoprost medicines like IYUZEH, when used in the eye (topical use):

- dizziness
- headache
- peeling skin over much of the body (toxic epidermal necrolysis)
- worsening of asthma
- shortness of breath (dyspnea)
- itching
- viral infection of the cornea (herpes keratitis)
- chest pain caused by interruptions in the heart’s blood supply, that can occur at rest (angina, unstable angina)
- awareness of heart rhythm (palpitations)
- chest pain

Tell your doctor if you have any side effect that bothers you or does not go away.

These are not all the possible side effects of IYUZEH. For more information, ask your doctor or pharmacist.

Call your doctor for medical advice about side effects. You may report side effects to FDA at 1-800-FDA-1088.

How should I store IYUZEH?

Before opening the foil pouches:

- Store the unopened foil pouches between 59°F to 77°F (15°C to 25°C).
- Do not open the foil pouch containing IYUZEH until you are ready to use the eye drops.

After opening the foil pouch:

- Store the opened foil pouch between 59°F to 77°F (15°C to 25°C), for up to 30 days.
- Write down the date of first opening the foil pouch in the space provided on the pouch.
- Throw away all unused IYUZEH single-dose containers in the opened foil pouch after 30 days.
- Keep the IYUZEH single-dose containers in their original foil pouch.

Keep IYUZEH and all medicines out of the reach of children.

General information about the safe and effective use of IYUZEH.

Medicines are sometimes prescribed for purposes other than those listed in a Patient Information leaflet. Do not use IYUZEH for a condition for which it was not prescribed. Do not give IYUZEH to other people, even if they have the same symptoms that you have. It may harm them.

You can ask your pharmacist or doctor for information about IYUZEH that is written for health professionals.

What are the ingredients in IYUZEH?

Active ingredients: latanoprost

Inactive ingredients: polyoxyl 40 hydrogenated castor oil, sorbitol, carbomer 974P, polyethylene glycol 4000, disodium edetate, sodium hydroxide (for pH-adjustment) and water.

Manufactured for: Thea Pharma Inc. Waltham, MA 02451.

All rights reserved.

U.S. Patent N°. 8,637,054. ©2021, Laboratoires Théa. All rights reserved. IYUZEH™ is a trademark of Laboratoires Théa.

This Patient Information has been approved by the U.S. Food and Drug Administration

Revised: 12/2022

Instructions for Use

Read these Instructions for Use before using your IYUZEH™ and each time you get a refill. There may be new information. This leaflet does not take the place of talking with your doctor about your medical condition or your treatment.

Important:

- IYUZEH is for the eye. Do not swallow IYUZEH.
- IYUZEH single-dose containers are packaged in a foil pouch.
- Do not dose the IYUZEH single-dose containers if the foil pouch is opened.
- Write down the date you open the foil pouch in the space provided on the pouch.
- Do not open the IYUZEH single-dose container until you are ready to use the eye drops.

Please follow these instructions to use IYUZEH:

Step 1. | Wash your hands and sit or stand comfortably.
Step 2. | Open the foil pouch containing a strip of 5 single-dose containers.; Write down the date of first opening on the foil pouch.
Step 3. | Take the strip of single-dose containers from the foil pouch; Break off one single-dose container from the strip; Place the unopened single-dose containers back in the foil pouch and fold the edge to close the pouch.
Step 4. | Hold the single-dose container upright.; Make sure that your IYUZEH medicine is in the bottom part of the single-dose container.; Twist open the top of the single-dose container as shown. Do not touch the tip after opening the container.
Step 5. | Tilt your head backwards. If you are unable to tilt your head, lie down.; Use your finger to gently pull down the lower eyelid of your affected eye.
Step 6. | Place the tip of the single-dose container close to, but not touching your eye.
Step 7. | Squeeze the single-dose container gently so that only one drop goes into your eye, then release the lower eyelid. If the drop misses your eye completely, try again.

- If your doctor has told you to use IYUZEH drops in both eyes, repeat Steps 5 to Step 7 for your other eye.
- Each single-dose container contains enough solution for both eyes.
- Throw away the single-dose container after use. Do not keep it to use it again. To lessen the chance of an infection, a new single-dose container must be opened each time you are ready to use IYUZEH.
- Place the unopened foil pouch with the unopened single-dose containers back in the carton. The unopened single-dose containers must be used within 30 days after opening the foil pouch.

Rx

Manufactured for: Thea Pharma Inc. Waltham, MA 02451.

All rights reserved.

U.S. Patent N°. 8,637,054. ©2021, Laboratoires Théa. All rights reserved. IYUZEH™ is a trademark of Laboratoires Théa.

This Patient Information and Instructions for Use have been approved by the U.S. Food and Drug Administration.

Approved: 12/2022

PACKAGE/LABEL PRINCIPAL DISPLAY PANEL

NDC 82584-003-30

IYUZEH™

(latanoprost ophthalmic
solution)

0.005%

30 single-dose containers
(0.2 mL each)

For Topical Ophthalmic Use - Rx only

Sterile

Contains no preservatives

Théa